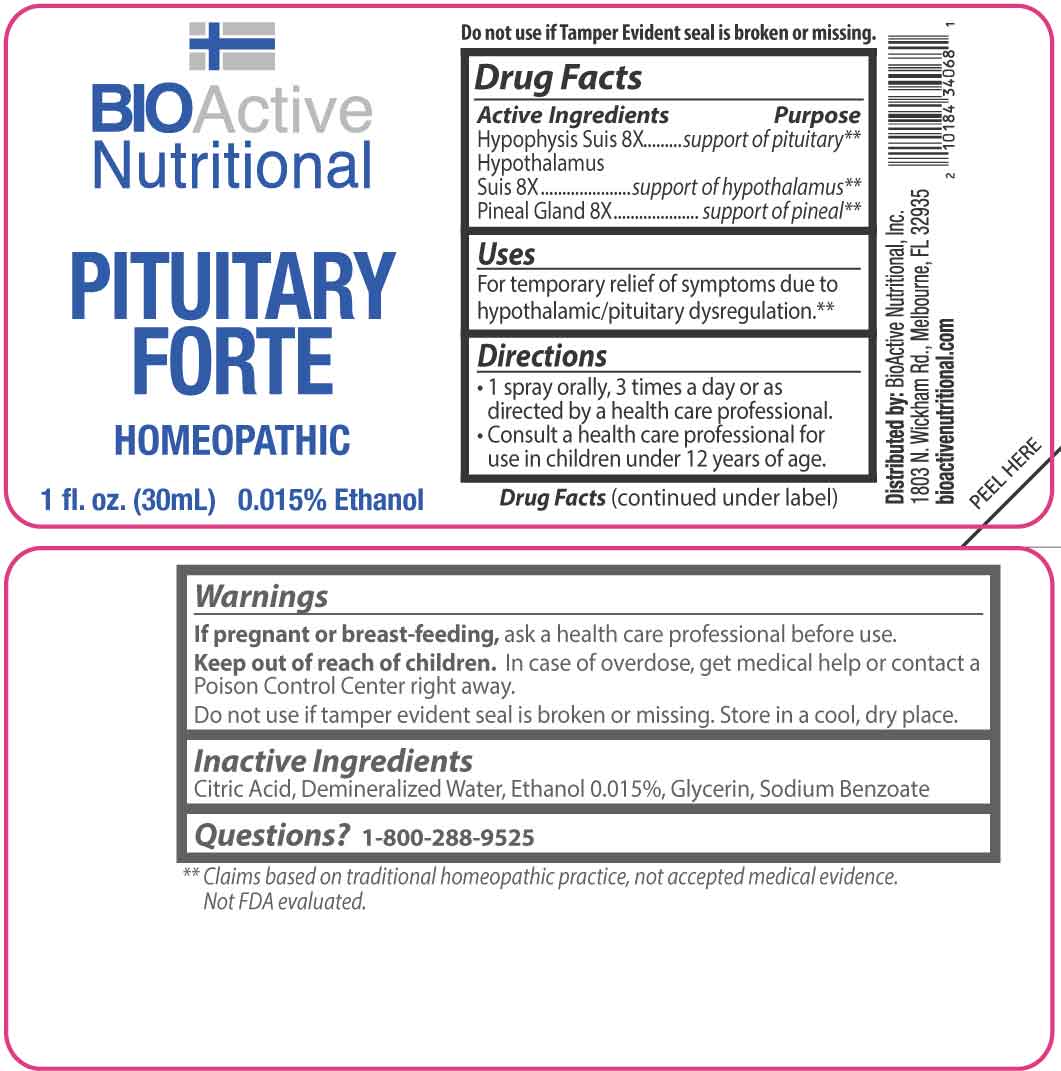 DRUG LABEL: Pituitary Forte
NDC: 43857-0665 | Form: SPRAY
Manufacturer: BioActive Nutritional, Inc.
Category: homeopathic | Type: HUMAN OTC DRUG LABEL
Date: 20260121

ACTIVE INGREDIENTS: SUS SCROFA PITUITARY GLAND 8 [hp_X]/1 mL; SUS SCROFA HYPOTHALAMUS 8 [hp_X]/1 mL; SUS SCROFA PINEAL GLAND 8 [hp_X]/1 mL
INACTIVE INGREDIENTS: CITRIC ACID MONOHYDRATE; GLYCERIN; SODIUM BENZOATE; WATER; ALCOHOL

DRUG FACTS:

ACTIVE INGREDIENTS:

Hypophysis Suis 8X, Hypothalamus Suis 8X, Pineal Gland 8X.

PURPOSE:

Hypophysis Suis – support of pituitary,** Hypothalamus Suis – support of hypothalamus,** Pineal Gland – support of pineal**

**Claims based on traditional homeopathic practice, not accepted medical evidence. Not FDA evaluated.

USES:

For temporary relief of symptoms dure to hypothalamic/pituitary dysregulation.**

**Claims based on traditional homeopathic practice, not accepted medical evidence. Not FDA evaluated.

WARNINGS:

If pregnant or breast-feeding, ask a health care professional before use.

Keep out of reach of children. In case of overdose, get medical help or contact a Poison Control Center right away.

Do not use if tamper evident seal is broken or missing.

Store in a cool, dry place.

KEEP OUT OF REACH OF CHILDREN:

In case of overdose, get medical help or contact a Poison Control Center right away.

DIRECTIONS:

• 1 spray orally, 3 times a day or as directed by a health care professional.

• Consult a health care professional for use in children under 12 years of age.

INACTIVE INGREDIENTS:

Citric Acid, Demineralized Water, Ethanol 0.015%, Glycerin, Sodium Benzoate

QUESTIONS:

Distributed by:

BioActive Nutritional, Inc.

1803 N. Wickham Rd.

Melbourne, FL 32935

bioactivenutritional.com

1-800-288-9525

PACKAGE LABEL DISPLAY:

BIOActive Nutritional

PITUITARY FORTE

HOMEOPATHIC

1 fl. oz. (30mL)